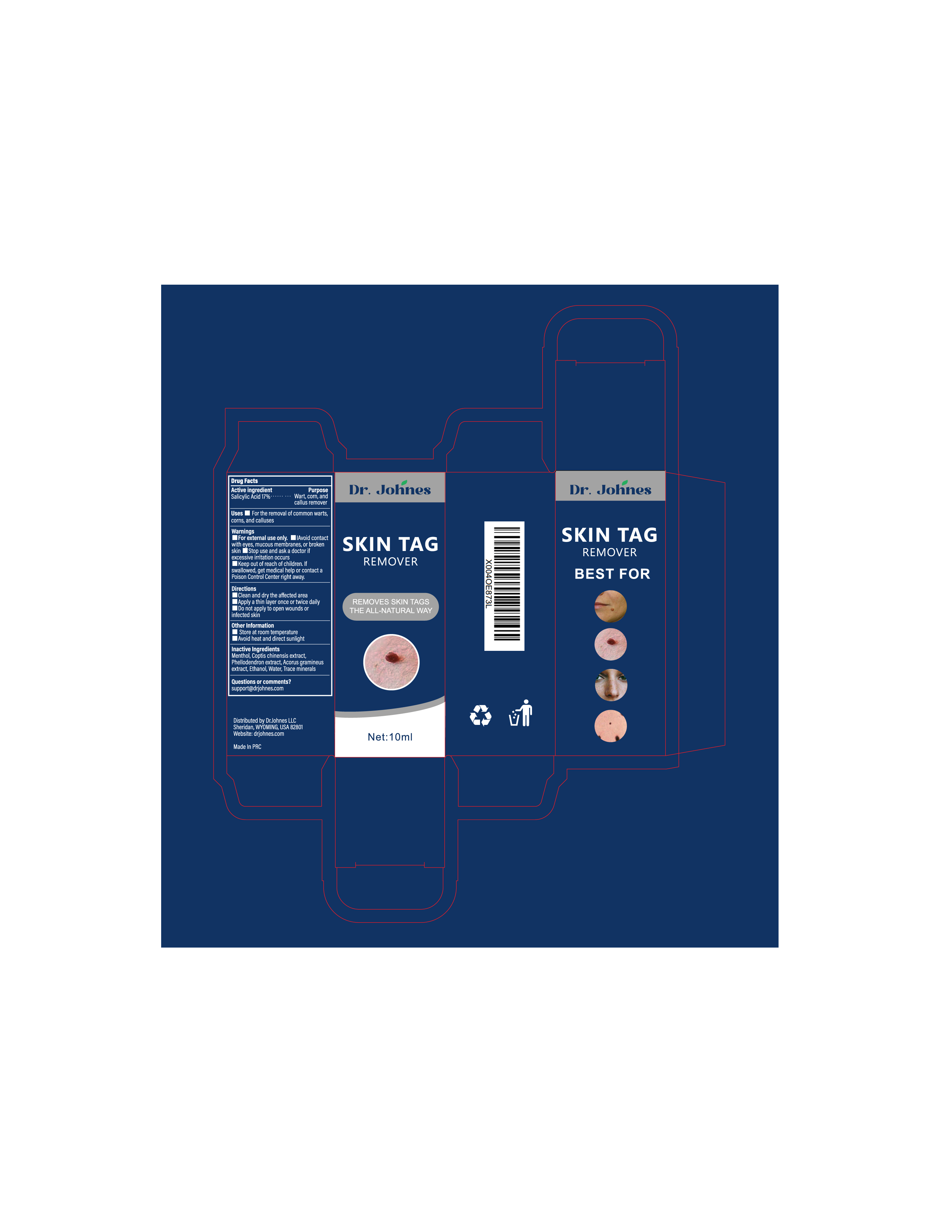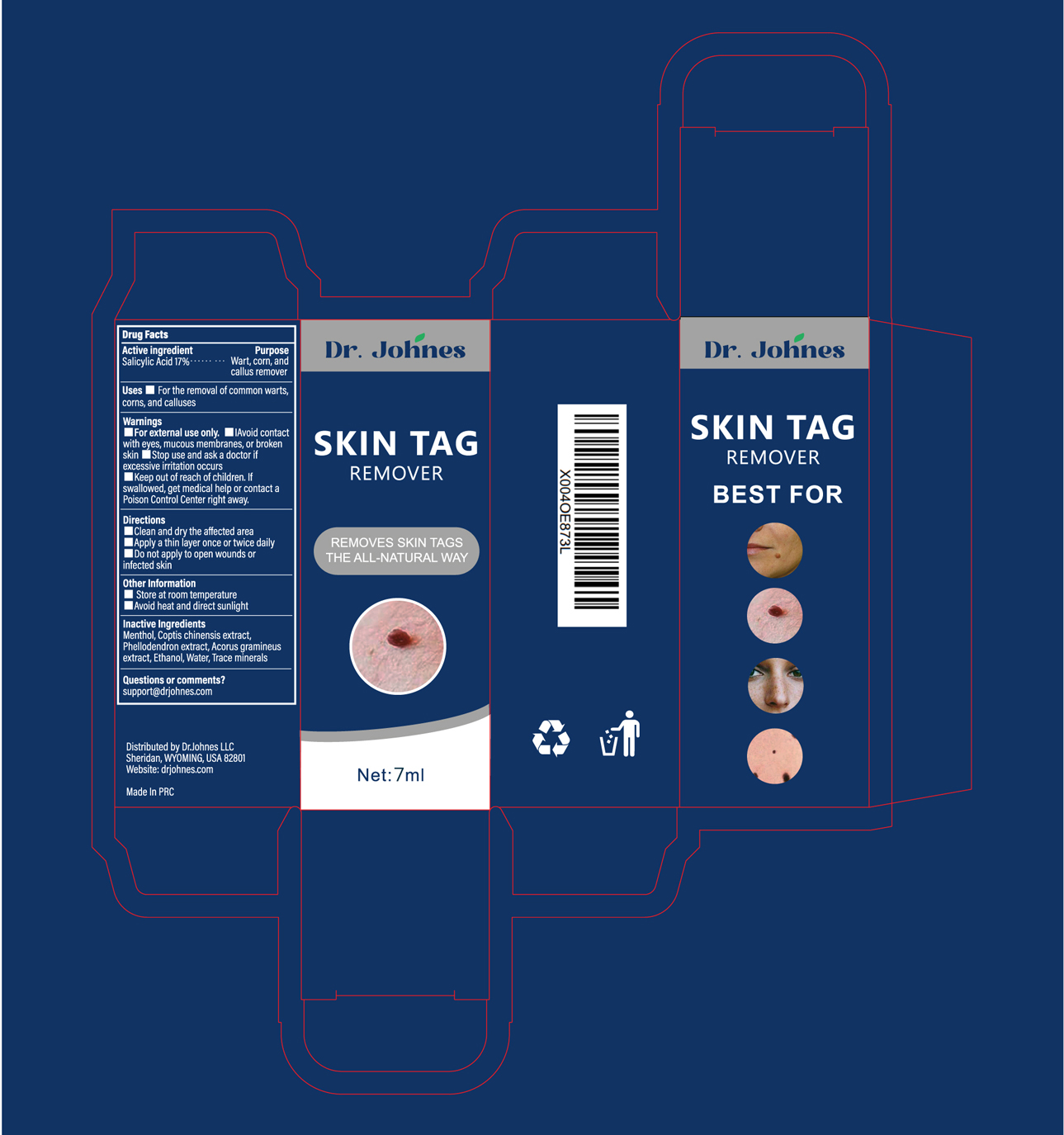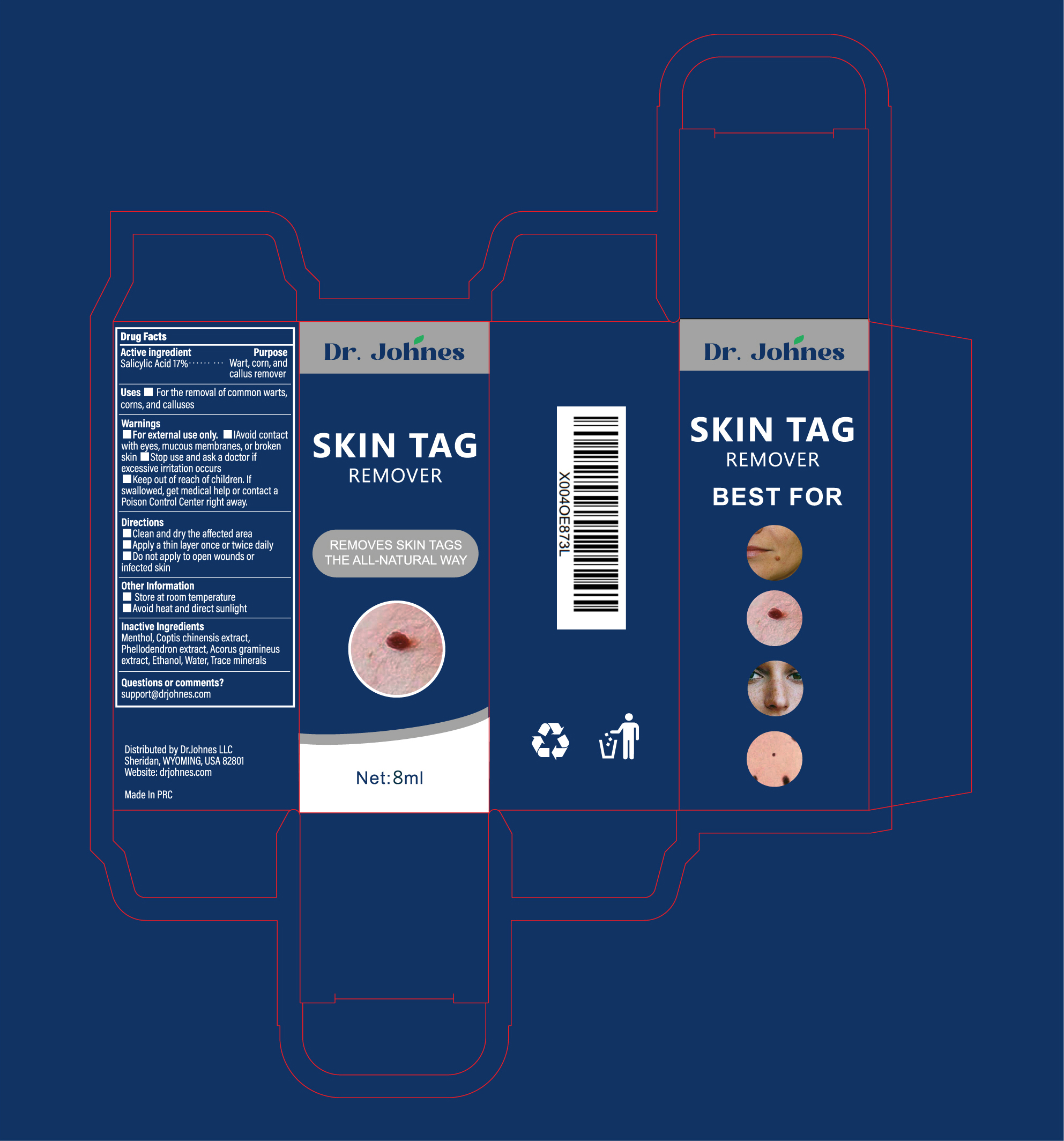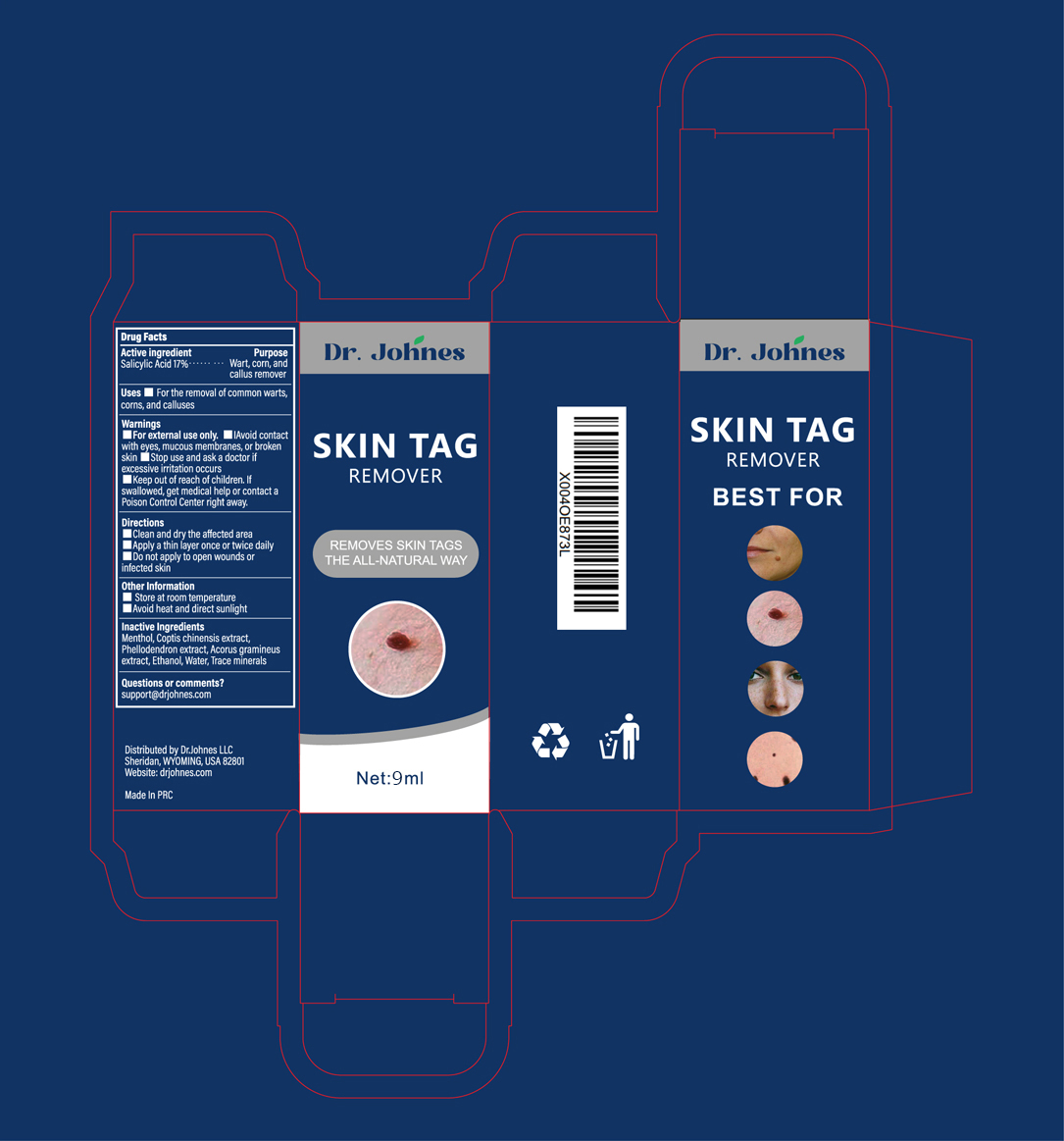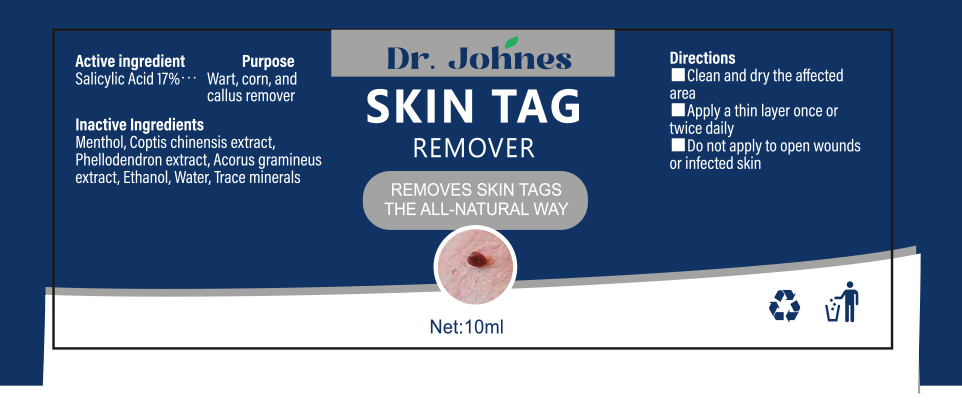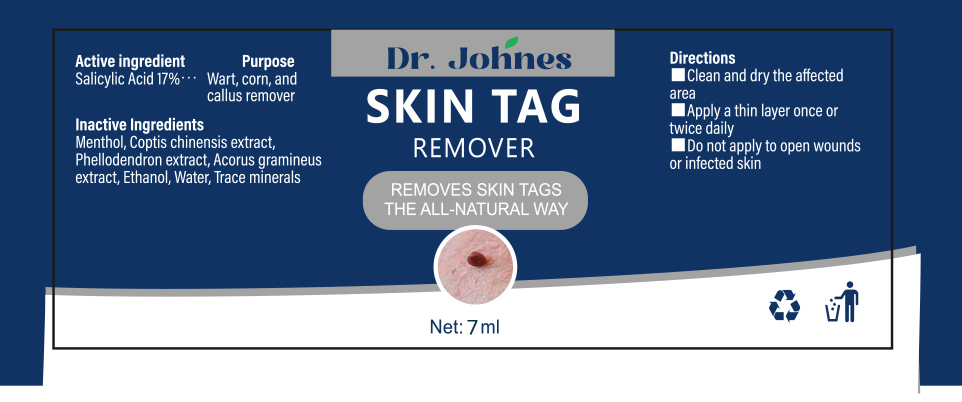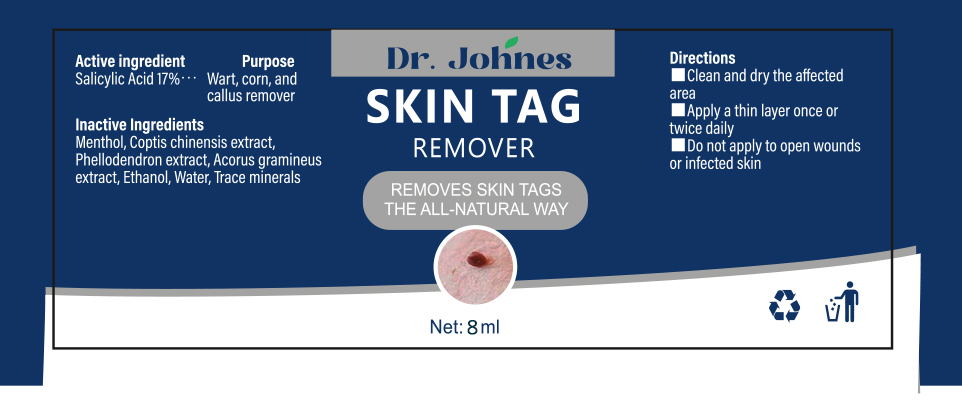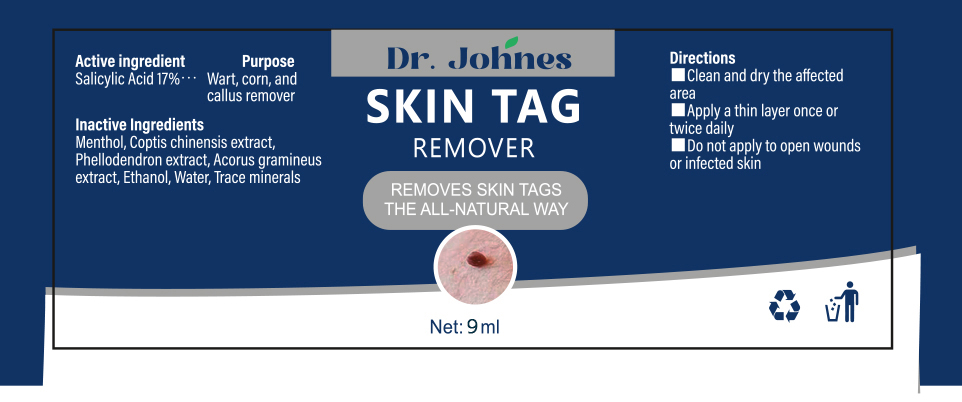 DRUG LABEL: Dr. Johne SKIN TAG REMOVER
NDC: 85818-001 | Form: SOLUTION
Manufacturer: Dr.Johnes LLC
Category: otc | Type: HUMAN OTC DRUG LABEL
Date: 20250618

ACTIVE INGREDIENTS: Salicylic Acid 170 mg/1 mL
INACTIVE INGREDIENTS: Menthol; COPTIS CHINENSIS ROOT; PHELLODENDRON CHINENSIS BARK; ACORUS GRAMINEUS ROOT; ALCOHOL; Water

Active ingredient:

1. Salicylic Acid 17%

PURPOSE

1. Wart, corn, and callus remover

INDICATIONS AND USAGE

Uses For the removal of common

1. warts
2. corns
3. calluses

WARNINGS

For external use only

Do not use:

- on mucous membranes, or broken skin
- Do not apply to open wounds or infected skin

When using this product

Avoid contact with eyes

Stop use and ask a doctor if

- excessive irritation occurs.

Keep out of reach of children.

If swallowed, get medical help or contact a Poison Control Center right away.

Directions:

- Clean and dry the affected area
- Apply a thin layer once or twice daily
- Do not apply to open wounds or infected skin

Other information:

- Store at room temperature
- Avoid heat and direct sunlight

Inactive ingredients:

- Menthol
- Coptis chinensis extract (COPTIS CHINENSIS ROOT)
- Phellodendron extract (PHELLODENDRON CHINENSIS BARK)
- Acorus gramineus extract (ACORUS GRAMINEUS ROOT)
- Ethanol (ALCOHOL)
- Water (WATER)

Questions or comments?

support@drjohnes.com

PACKAGE LABEL.PRINCIPAL DISPLAY PANEL

Available in 7 mL, 8 mL, 9 mL, and 10 mL tubes. All packages look the same externally, with the only variation being fill volume.